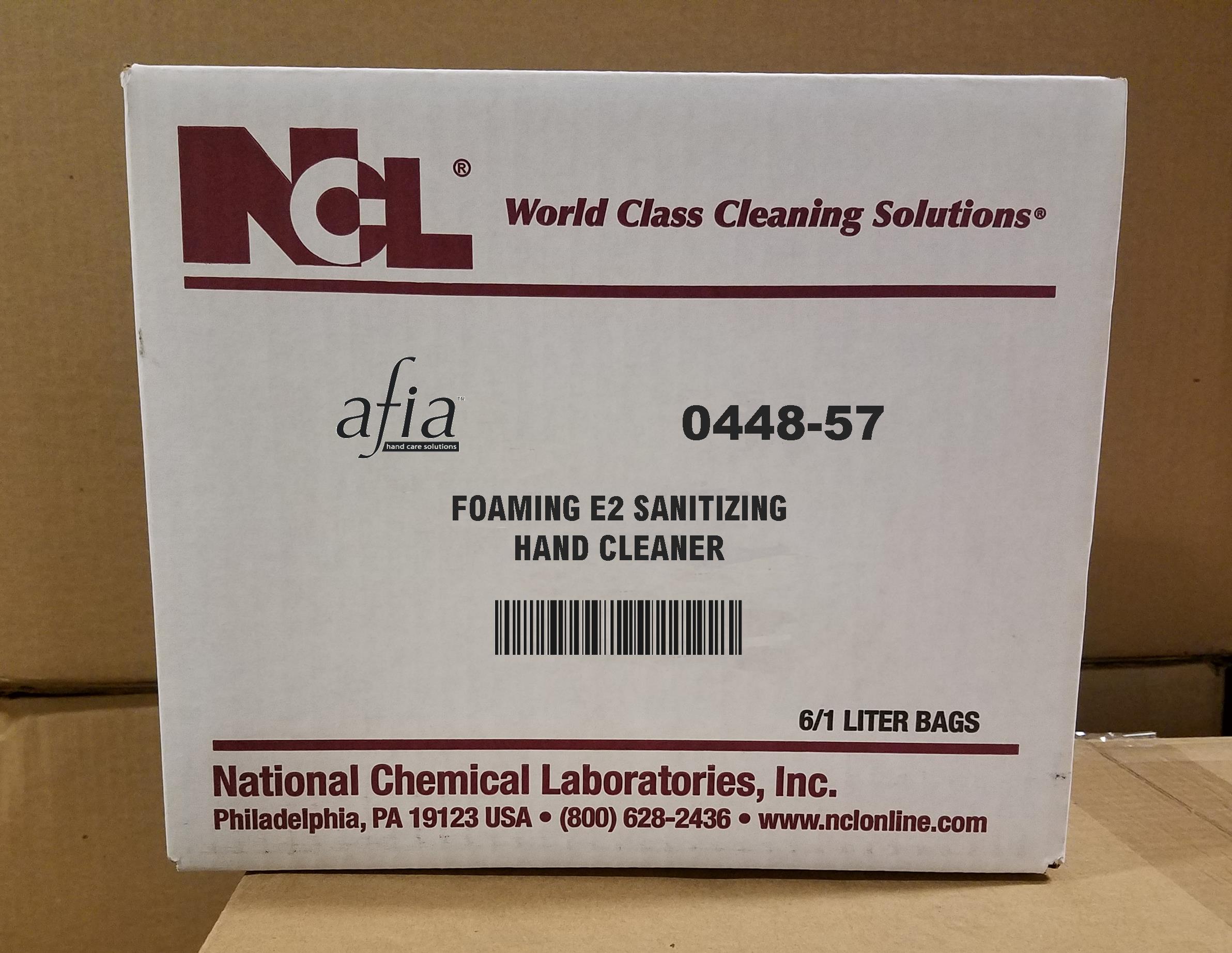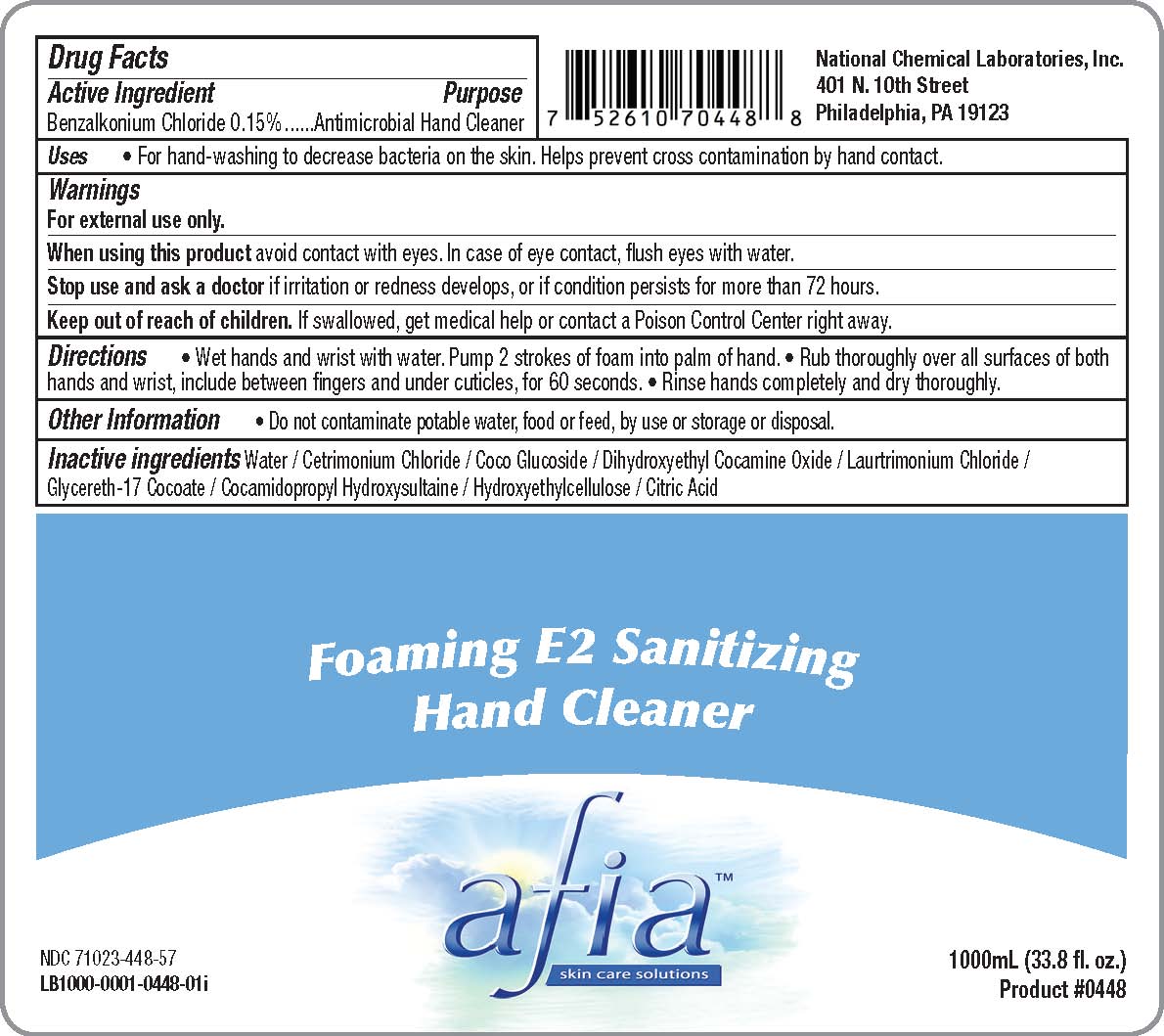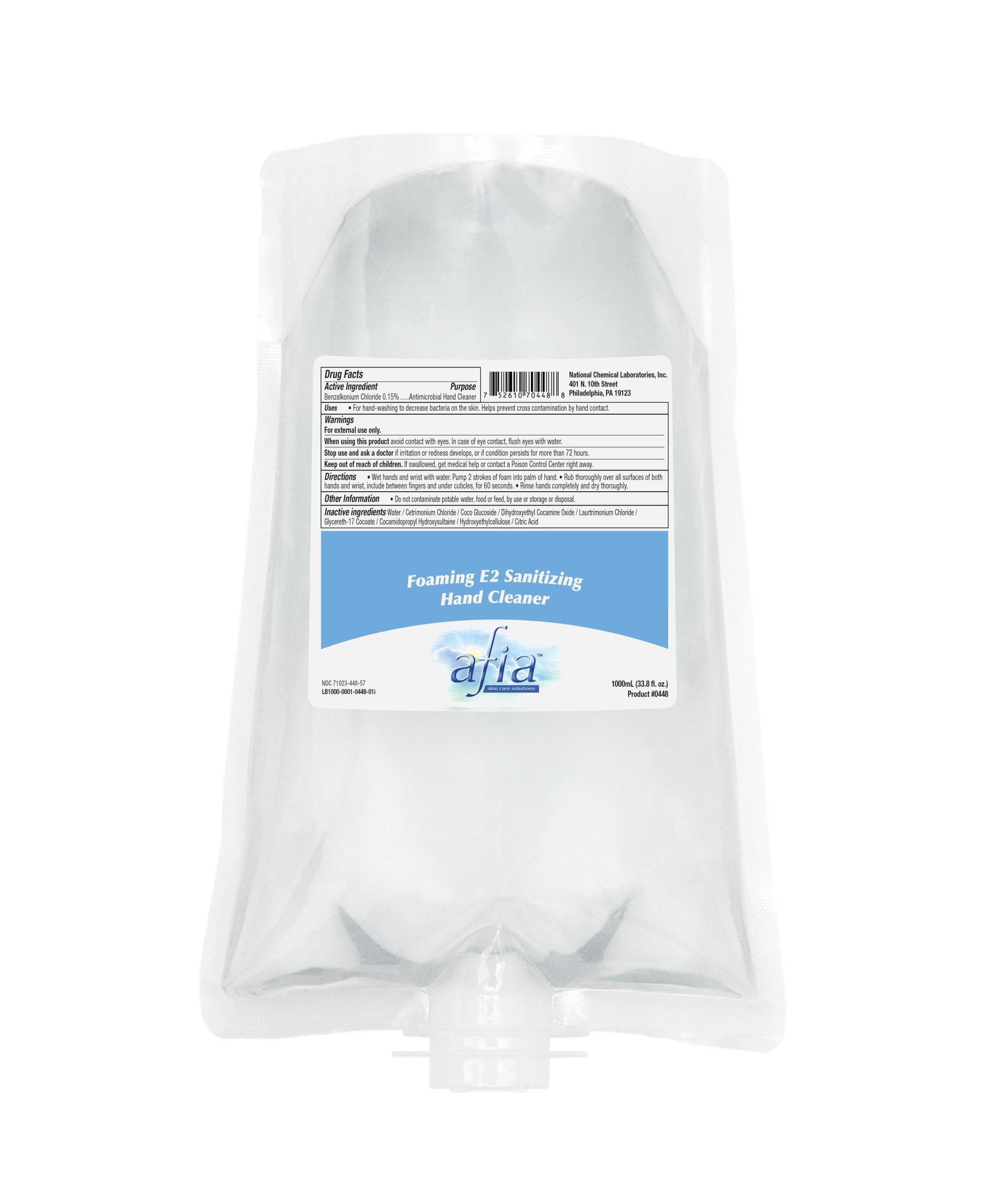 DRUG LABEL: Afia Foaming E2 Sanitizing Hand Cleaner
NDC: 71023-448 | Form: SOAP
Manufacturer: National Chemical Laboratories, Inc.
Category: otc | Type: HUMAN OTC DRUG LABEL
Date: 20170118

ACTIVE INGREDIENTS: BENZALKONIUM CHLORIDE 1 mg/1 mL
INACTIVE INGREDIENTS: DIHYDROXYETHYL COCAMINE OXIDE; HYDROXYETHYL CELLULOSE (5000 MPA.S AT 1%); GLYCERETH-17 COCOATE; WATER; COCO GLUCOSIDE; LAURTRIMONIUM CHLORIDE; ANHYDROUS CITRIC ACID; CETRIMONIUM CHLORIDE; COCAMIDOPROPYL HYDROXYSULTAINE

Listing of Afia Foaming E2 Sanitizing Hand Cleaner

Drug Facts

Active Ingredient. Purpose

Benzalkonium Chloride 0.15%...........Antimicrobial hand Cleaner

Uses

- Uses • For hand-washing to decrease bacteria on the skin. Helps prevent cross contamination by hand contact.

Warnings:

Warnings For external use only.

When using this product avoid contact with eyes. In case of eye contact, flush eyes with water. Stop use and ask a doctor if irritation or redness develops, or if condition persists for more than 72 hours.

Keep out of reach of children. If swallowed, get medical help or contact a Poison Control Center right away.

Directions

• Wet hands and wrist with water. Pump 2 strokes of foam into palm of hand. • Rub thoroughly over all surfaces of both hands and wrist, include between fingers and under cuticles, for 60 seconds. • Rinse hands completely and dry thoroughly.

Inactive ingredients

Water / Cetrimonium Chloride / Coco Glucoside / Dihydroxyethyl Cocamine Oxide / Laurtrimonium Chloride / Glycereth-17 Cocoate / Cocamidopropyl Hydroxysultaine / Hydroxyethylcellulose / Citric Acid

Uses

For hand-washing to decrease bacteria on the skin. Helps prevent cross contamination by hand contact.

Keep out of reach of children. If swallowed, get medical help or contact a Poison Control Center right away.

PACKAGE LABEL

Afia Foaming E2 Sanitizing Hand Cleaner